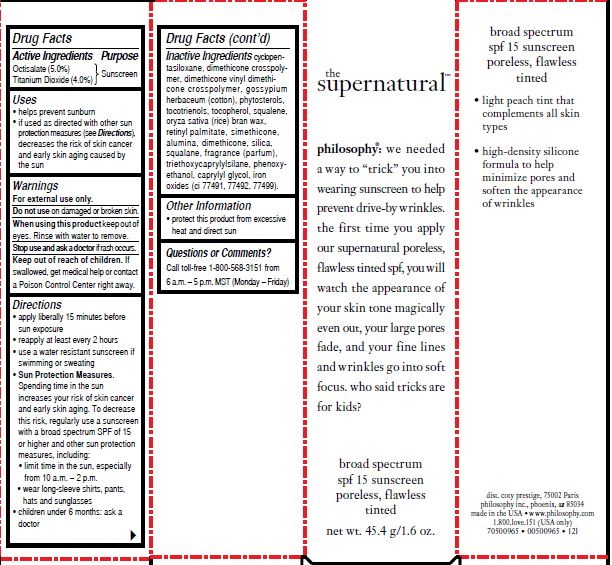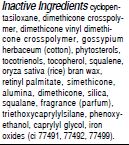 DRUG LABEL: supernatural poreless tint spf 15
NDC: 50184-1066 | Form: CREAM
Manufacturer: PHILOSOPHY INC.
Category: otc | Type: HUMAN OTC DRUG LABEL
Date: 20200211

ACTIVE INGREDIENTS: TITANIUM DIOXIDE 4 g/100 g; OCTISALATE 5 g/100 g
INACTIVE INGREDIENTS: SQUALANE; PHENOXYETHANOL; CAPRYLYL GLYCOL; DIMETHICONE CROSSPOLYMER (450000 MPA.S AT 12% IN CYCLOPENTASILOXANE); SQUALENE; TRIETHOXYCAPRYLYLSILANE; TOCOTRIENOLS

supernatural poreless tint spf 15

Active Ingredients

Octisalate (5.0%)

Titanium Dioxide (4.0%)

Purpose

Sunscreen

Uses

helps prevent sunburn

if used as directed with other sun protection measures (see Directions), decreases the risk of skin cancer and early skin aging caused by the sun

Warnings

For external use only.

Do not use

on damaged or broken skin.

When using this product

keep out of eyes. Rinse with water to remove.

Stop use and ask a doctor

if rash occurs.

Keep out of reach of children.

If swallowed, get medical help or contact a Poison Control Center right away.

Directions

apply liberally 15 minutes before sun exposure

reapply at least every 2 hours

use a water resistant sunscreen if swimming or sweating

Sun Protection Measures.

Spending time in the sun increases your risk of skin cancer and early skin aging. To decrease this risk, regularly use a sunscreen with a broad spectrum SPF of 15 or higher and other sun protection measures, including:

limit time in the sun, especially from 10 a.m.-2 p.m.

wear long-sleeve shirts, pants, hats and sunglasses

children under 6 months: ask a doctor

Other Information

protect this product from excessive heat and direct sun

Questions or Comments?

Call toll-free 1-800-568-3151 from 6 a.m.-5 p.m. MST (Monday-Friday)

PACKAGE LABEL

the

supernatural

philosophy: we needed

a way to "trick" you into

wearing sunscreen to help

prevent drive-by wrinkles.

the first time you apply

our supernatural poreless,

flawless tinted spf, you will

watch the appearance of

your skin tone magically

even out, your large pores

fade, and your fine lines

and wrinkles go into soft

focus. who said tricks are

for kids?

broad spectrum

spf 15 sunscreen

poreless, flawless

tinted